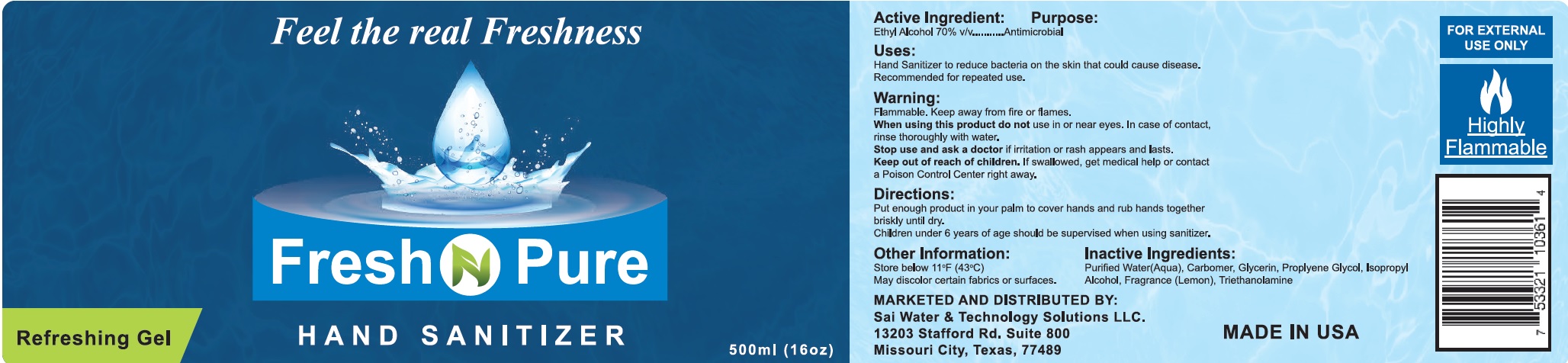 DRUG LABEL: Fresh N Pure Hand Sanitizer
NDC: 81501-000 | Form: GEL
Manufacturer: Sai Water & Technology Solution LLC
Category: otc | Type: HUMAN OTC DRUG LABEL
Date: 20210211

ACTIVE INGREDIENTS: ALCOHOL 70 mL/100 mL
INACTIVE INGREDIENTS: WATER; CARBOMER HOMOPOLYMER, UNSPECIFIED TYPE; GLYCERIN; PROPYLENE GLYCOL; ISOPROPYL ALCOHOL; TROLAMINE

Fresh N Pure Hand Sanitizer

Active Ingredient:

Ethyl Alcohol 70% v/v

Purpose:

Antimicribial

Uses:

Hand Sanitizer to help reduce bacteria on the skin that could cause disease. Recommended for repeated use.

Warnings:

Flammable. Keep away from fire or flames.

When using this product

do not use in or near eyes. In case of contact, rinse thoroughly with water.

Stop use and ask a doctor

if irritation or rash appears and lasts.

Keep out of reach of children.

If swallowed, get medical help or contact a Poison control Center right away.

Directions:

- Put enough product in your palm to cover hands and rub hands together briskly until dry.
- Children under 6 years of age should be supervised when using sanitizer.

Other Information:

- Store below 110°F (43°C)
- May discolor some fabrics or surfaces.

Inactive Ingredients:

Purified Water(Aqua), Carbomer, Glycerin, Propylene Glycol, Isopropyl Alcohol, Fragrance (Lemon), Triethanolamine